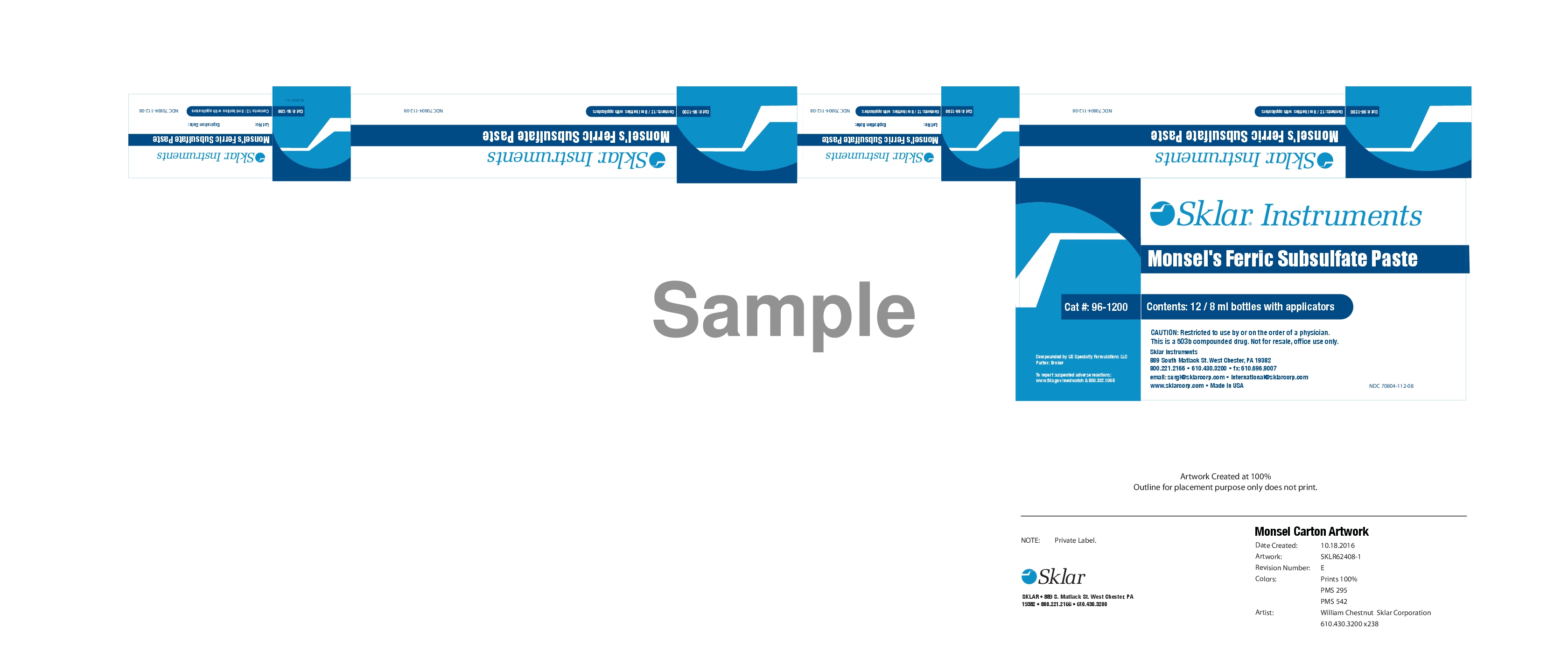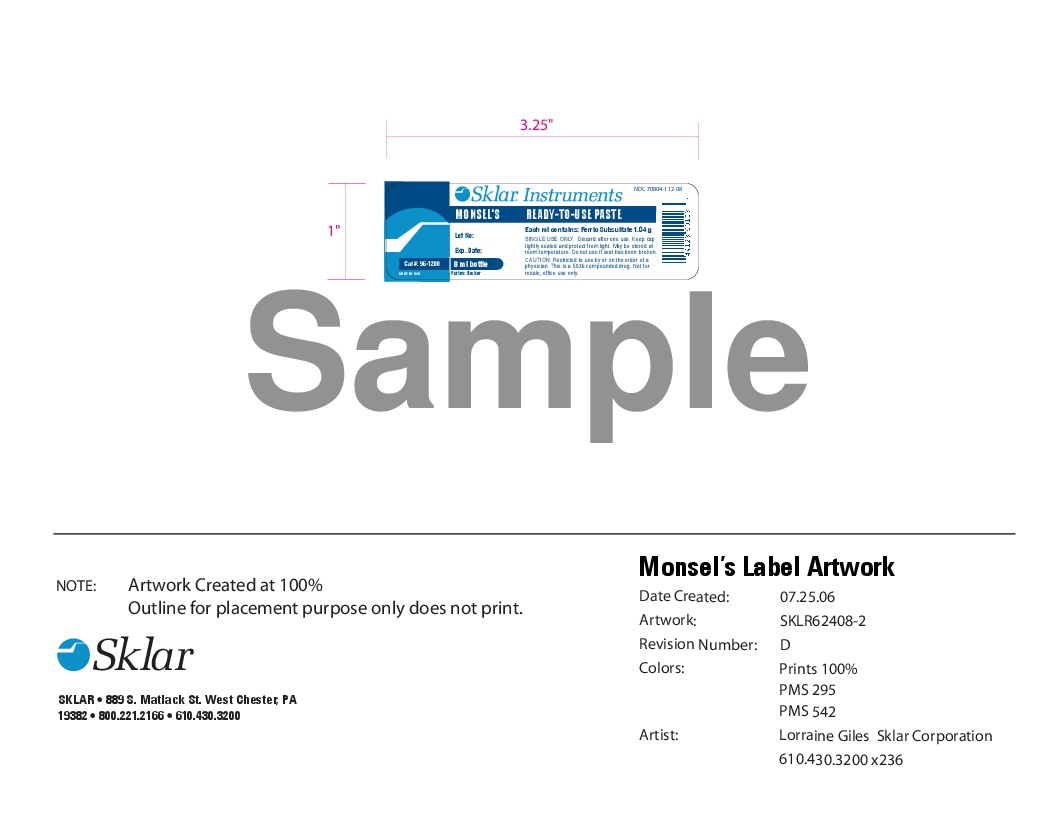 DRUG LABEL: MONSEL
NDC: 70804-112 | Form: PASTE
Manufacturer: PURTEX INC
Category: prescription | Type: HUMAN PRESCRIPTION DRUG LABEL
Date: 20191111

ACTIVE INGREDIENTS: FERRIC SUBSULFATE 1 g/1 1

Restricted to use by or on the order of a licensed Physician. Keep cap tightly sealed and protect from light